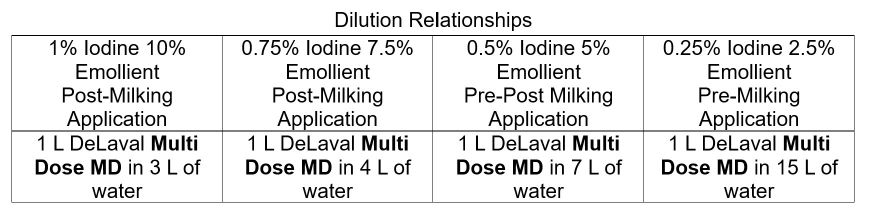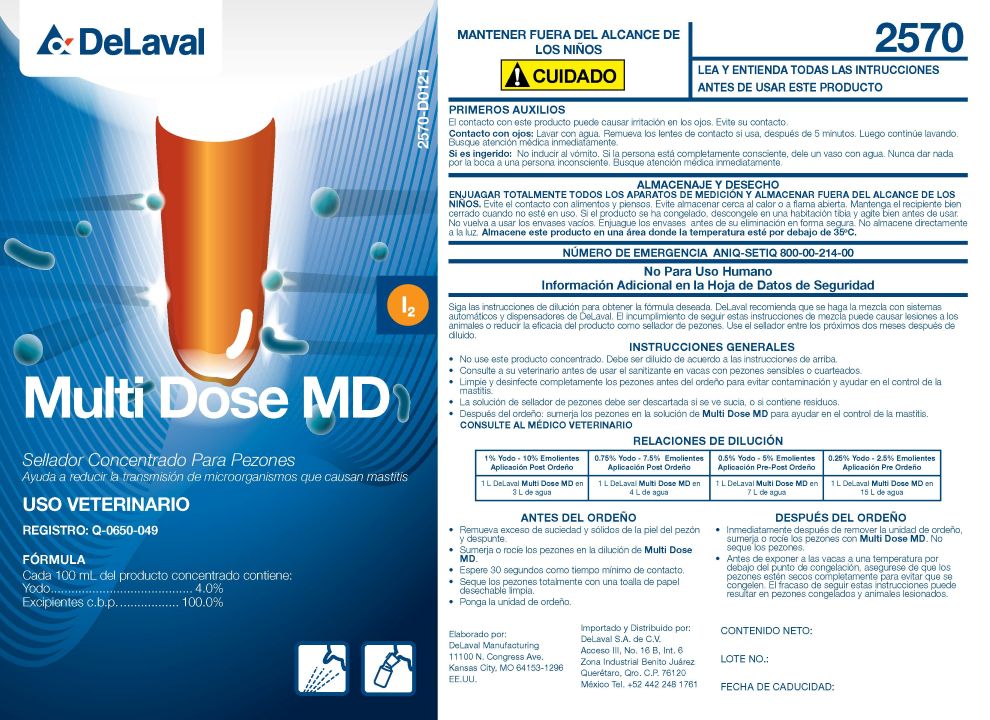 DRUG LABEL: Multi Dose MD
NDC: 55756-570 | Form: SOLUTION, CONCENTRATE
Manufacturer: DeLaval
Category: animal | Type: OTC ANIMAL DRUG LABEL
Date: 20251210

ACTIVE INGREDIENTS: IODINE 4000 mg/1 L
INACTIVE INGREDIENTS: GLYCERIN; C9-11 PARETH-8; POLOXAMER 335; PROPYLENE GLYCOL; SODIUM IODIDE; ANHYDROUS CITRIC ACID; SODIUM HYDROXIDE; WATER

Multi Dose MD™

PURPOSE

Concentrated Teat Sealant
Helps reduce the transmission of microorganisms that cause mastitis

Veterinary Use

Registration Q-0650-049

ACTIVE INGREDIENTS
Iodine........................................4.0% W/V

OTHER INGREDIeNT

Excipients....................sufficient quality for .....100%

KEEP OUT OF REACH OF CHILDREN
CAUTION

READ AND UNDERSTAND ALL INSTRUCTIONS BEFORE USING THIS PRODUCT

FIRST AID
Contact with product may cause irritation. Avoid contact.
Eye Contact: Rinse with water. Remove contact lenses, if present, after first 5 minutes. Then continue rinsing. Seek medical attention immediately.
If Swallowed: Do not induce vomiting. If victim is fully conscious, give them a glass of water. Never give anything else.

STORAGE AND DISPOSAL
THOROUGHLY RINSE ALL MEASURING DEVICES AND STORE OUT OF REACH OF CHILDREN. Avoid contact with food or animal feed. Avoid storing near heat or open flame. Keep container tightly closed when not in use. If product has frozen, thaw in a warm room and shake well before use. Do not reuse empty container. Rinse containers before safe disposal. Do not store in direct sunlight. Store this product in an area where the temperatures is below 35°C.

ANIQ-SETIQ Emergency Number 01-800-00-214-00

Not for Human Use
Additional Information in the Safety Data Sheet

Follow the dilution instructions to obtain the desired formula. DeLaval recommends mixing with DeLaval's automatic systems and dispensers. Failure to follow these mixing instructions could cause injury to animals or reduce the effectiveness as a teat sealant. Use the sealant within two months of dilution.

DOSAGE AND ADMINISTRATION

GENERAL INSTRUCTIONS

- Do not use this product concentrated. It must be diluted according to the instructions.
- Consult your veterinarian before using the sanitizer on cows with sensitive or cracked teats.
- Thoroughly clean and disinfect teats before milking to prevent contamination and help control mastitis.
- The teat sealant solution should be discarded if it appears dirty or contains residue.
- After milking: Dip teats in Multi Dose MD solution to help control mastitis.

BEFORE MILKING

- Remove excess dirt and solids from the teat skin and trim the teat ends.
- Immerse or spray the teats in the Multi Dose MD™dilution.
- Wait a minimum of 30 second for contact time.
- Dry the teats thoroughly with a clean, disposable paper towel.
- Attach the milker unit.

AFTER MILKING

- Immediately after removing the milking unit, dip or spray the teats with Multi Dose MD™. Do not dry the teats
- Before exposing cows to temperatures below freezing, ensure that the teats are completely dry to prevent frostbite. Failure to follow these instructions may result in frontbite and injury to the animals.

NET CONTENTS: US GAL. (L)

LOT NO.:

EXP. DATE:

Prepared By:

DeLaval Manufacturing
11100 N. Congress Avenue
Kansas City, MO 64153 USA

Imported and Distributed By:

DeLaval S.A de C.V.

Acceso III No 16-B, Int 6 Zona

Zona Industrial Benito Juarez

Queretaro,Qro. C.P. 76120

Mexico Te. +52 442 248 1761